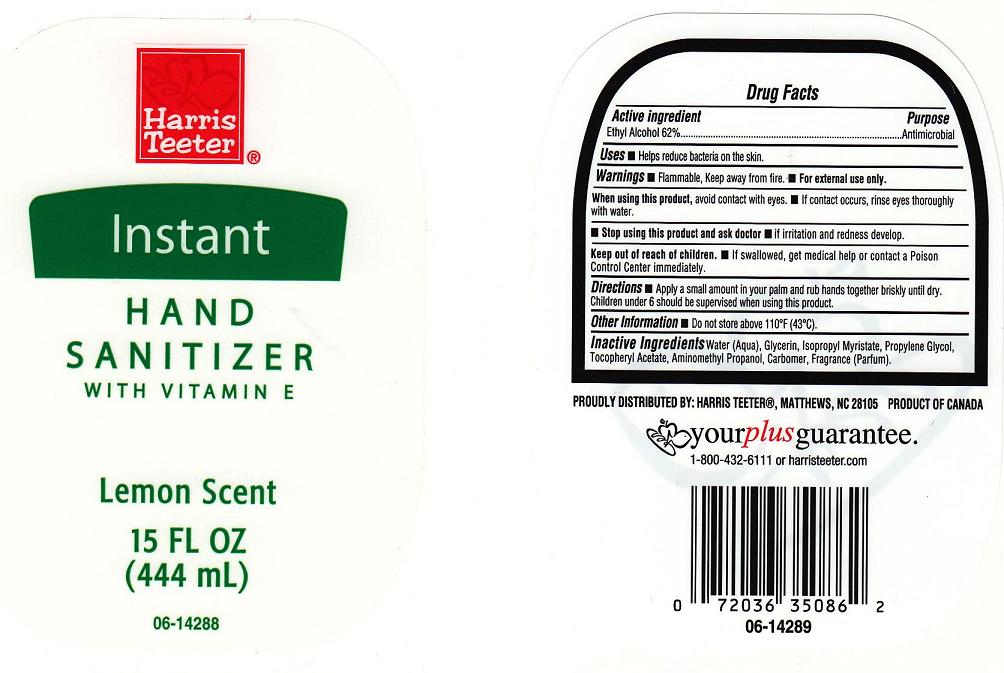 DRUG LABEL: Harris Teeter 
NDC: 72036-227 | Form: GEL
Manufacturer: Harris Teeter
Category: otc | Type: HUMAN OTC DRUG LABEL
Date: 20101007

ACTIVE INGREDIENTS: ALCOHOL 62 mL/100 mL
INACTIVE INGREDIENTS: WATER; GLYCERIN; ISOPROPYL MYRISTATE; PROPYLENE GLYCOL ALGINATE; .ALPHA.-TOCOPHEROL ACETATE, D-; AMINOMETHYLPROPANOL; CARBOMER 934

Active Ingredient

Ethyl Alcohol 62%

Purpose

Antibacterial

Warnings

Flammable, keep away from fire.For external use only.

When using this product

- Avoid contact with eyes. If contact occurs, rinse with water.

Stop using this product and ask doctor if

- irritation or redness develops and lasts.

Keep out of reach of children

In case of accidental ingestion, get medical help or contact a Poison Control Center immediately.

Directions

Apply a small amount in your palm and rub hands together briskly until dry. Children under 6 should be supervised when using this product..

Uses

Helps reduce bacteria on the skin

Inactive Ingredients

Water (Aqua), Glycerin, Isopropyl Myristate, Propylene Glycol, Tocopheryl Acetate, Aminomethyl Propanol, Carbomer, Fragrance (Parfum)

Package Front and Back Labels

ht.jpg